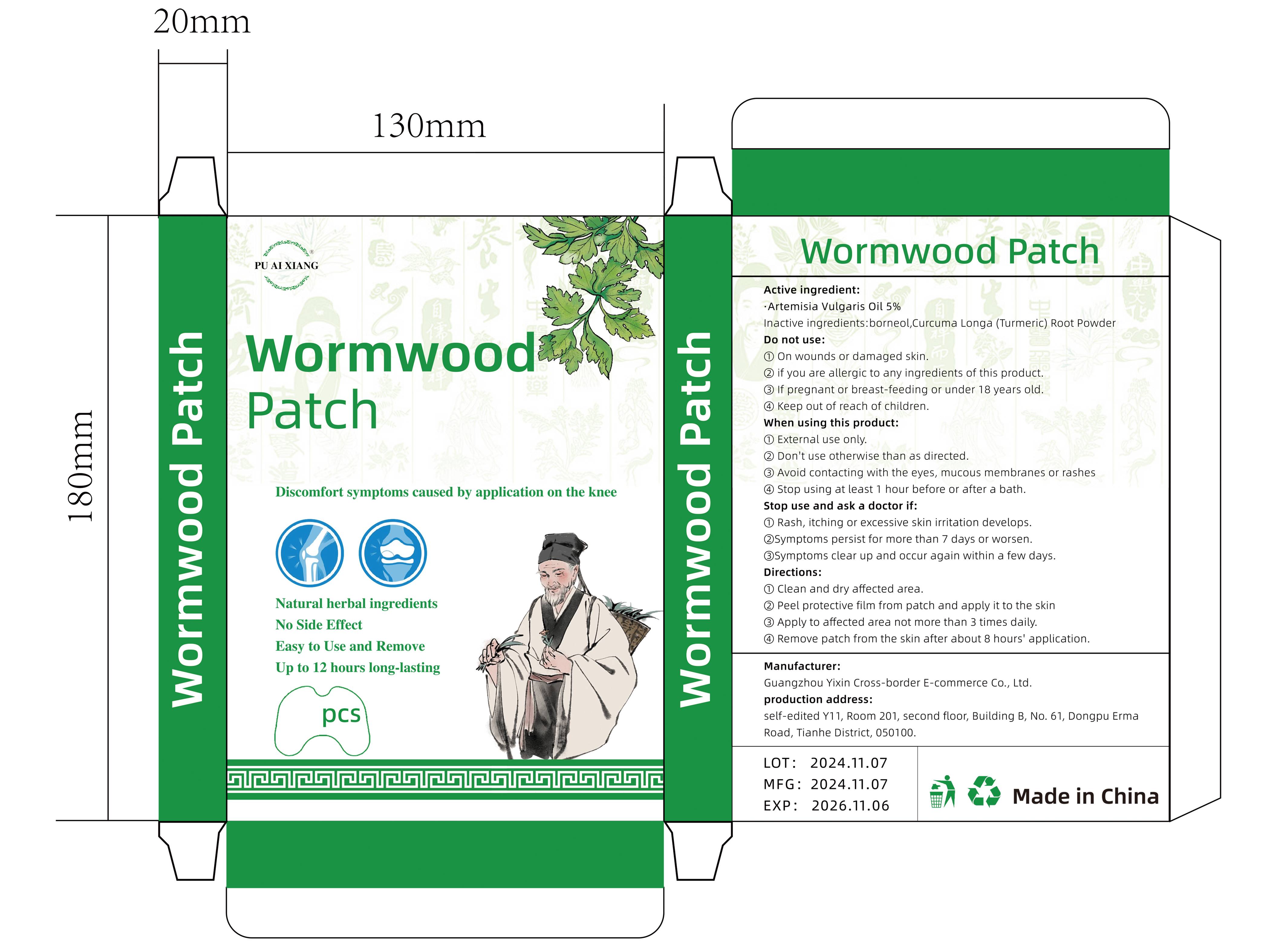 DRUG LABEL: PUAIXIANG Wormwood patch
NDC: 84778-067 | Form: PATCH
Manufacturer: Guangzhou Yixin Cross-border E-commerce Co., Ltd.
Category: otc | Type: HUMAN OTC DRUG LABEL
Date: 20241203

ACTIVE INGREDIENTS: ARTEMISIA VULGARIS OIL 1 g/1 g
INACTIVE INGREDIENTS: BORNEOL; CURCUMA LONGA (TURMERIC) RHIZOME EXTRACT

Active ingredients

ARTEMISIA VULGARIS OIL 5%

Purpose

Discomfort symptoms caused by application on the knee

USES

When using this product
①External use only.
② Don't use otherwise than as directed.
③Avoid contacting with the eyes, mucous membranes or rashes
stop using at least 1 hour before or after a bath.

WARNINGS

①On wounds or damaged skin.
②if you are allergic to any ingredients of this product.
③lf pregnant or breast-feeding or under 18 years old.

DOSAGE AND ADMINISTRATION SECTION

①Clean and dry affected area.
②Peel protective film from patch and apply it to the skin
③Apply to affected area not more than 3 times daily.
④Remove patch from the skin after about 8 hours' application.

DO NOT USE SECTION

①On wounds or damaged skin.
② if you are allergic to any ingredients of this product.
③If pregnant or breast-feeding or under 18 years old.

WHEN USING SECTION

①External use only.
②Don't use otherwise than as directed.
③Avoid contacting with the eyes, mucous membranes or rashes
④stop using at least 1 hour before or after a bath.

STOP USE

①Rash,itching or excessive skin irritation develops.
②Symptoms persist for more than 7 days or worsen.
③Symptoms clear up and occur again within a few days.

KEEP OUT OF REACH OF CHILDREN.

INACTIVE INGREDIENT

borneol
Curcuma Longa (Turmeric) Root Powder